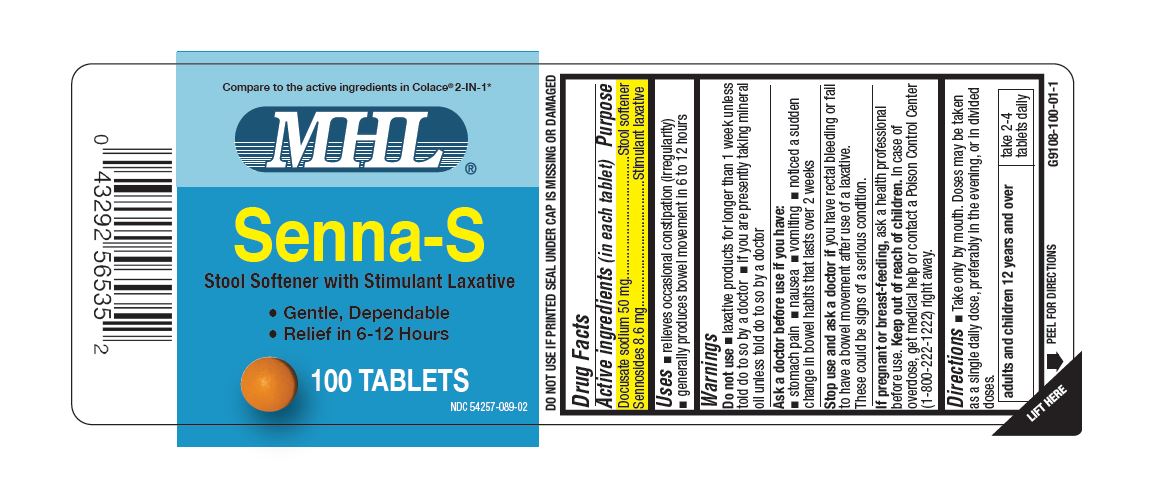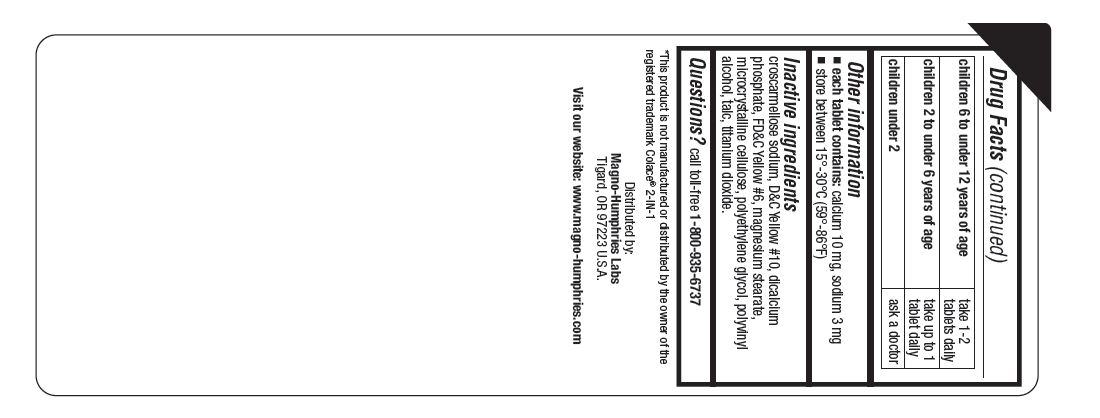 DRUG LABEL: Senna S
NDC: 54257-089 | Form: TABLET
Manufacturer: Magno-Humphries, Inc.
Category: otc | Type: HUMAN OTC DRUG LABEL
Date: 20231027

ACTIVE INGREDIENTS: DOCUSATE SODIUM 50 mg/1 1; SENNOSIDES 8.6 mg/1 1
INACTIVE INGREDIENTS: CROSCARMELLOSE SODIUM; D&C YELLOW NO. 10; ANHYDROUS DIBASIC CALCIUM PHOSPHATE; FD&C YELLOW NO. 6; MAGNESIUM STEARATE; MICROCRYSTALLINE CELLULOSE; POLYETHYLENE GLYCOL, UNSPECIFIED; POLYVINYL ALCOHOL, UNSPECIFIED; TALC; TITANIUM DIOXIDE

Senna-S

Active ingredients (in each tablet)

Docusate sodium 50 mg

Sennosides 8.6 mg

Purpose

Stool softener

Stimulant laxative

Uses

- relieves occasional constipation (irregularity)
- generally produces bowel movement in 6 to 12 hours

Warnings

Do not use

- laxative products for longer than 1 week unless told do to so by a doctor
- if you are presently taking mineral oil unless told do to so by a doctor

Ask a doctor before use if you have

- stomach pain
- nausea
- vomiting
- noticed a sudden change in bowel habits that lasts over 2 weeks

Stop use and ask a doctor if

you have rectal bleeding or fail to have a bowel movement after use of a laxative. These could be signs of a serious condition.

If pregnant or breast-feeding,

ask a health professional before use.

Keep out of reach of children.

In case of overdose, get medical help or contact a Poison Control Center (1-800-222-1222) right away.

Directions

- Take only by mouth. Doses may be taken as a single daily dose, preferably in the evening, or in divided doses.

adults and children 12 years and over | take 2-4 tablets daily
children 6 to under 12 years of age | take 1-2 tablets daily
children 2 to under 6 years of age | take up to 1 tablet daily
children under 2 | ask a doctor

Other information

- each tablet contains: calcium 10 mg, sodium 3 mg
- store between 15°-30°C (59°-86°F)

Inactive ingredients

croscarmellose sodium, D&C Yellow #10, dicalcium phosphate, FD&C Yellow #6, magnesium stearate, microcrystalline cellulose, polyethylene glycol, polyvinyl alcohol, talc, titanium dioxide.

Questions?

call toll-free 1-800-935-6737